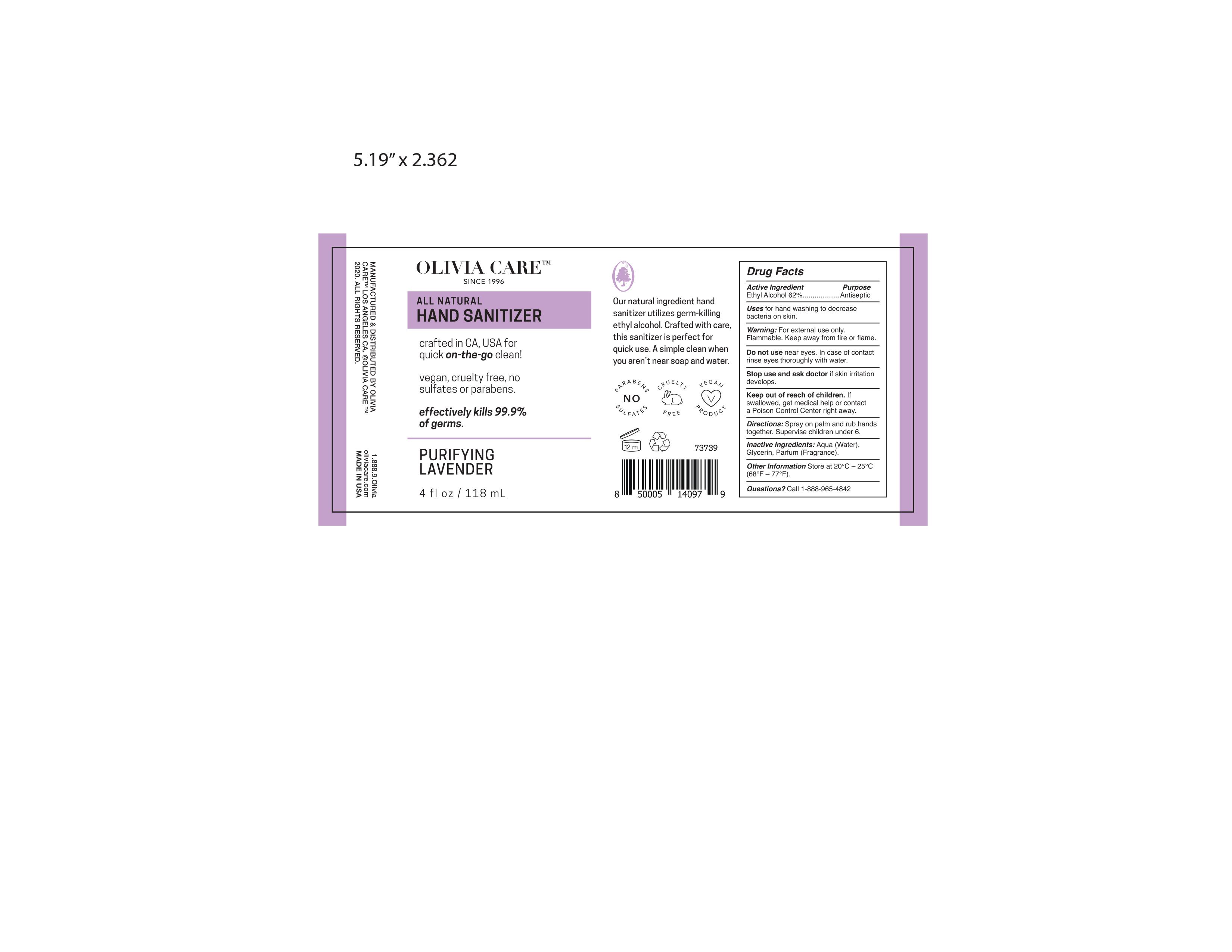 DRUG LABEL: Hand Sanitizer
NDC: 73739-000 | Form: SPRAY
Manufacturer: Olivia Care
Category: otc | Type: HUMAN OTC DRUG LABEL
Date: 20240108

ACTIVE INGREDIENTS: ALCOHOL 80 mL/100 mL
INACTIVE INGREDIENTS: GLYCERIN 1.45 mL/100 mL; WATER

DOSAGE AND ADMINISTRATION

Place enough product on hands to cover all surfaces. Rub hands together until dry.
Supervise children under 6 years of age when using this product to avoid swallowing.

WARNINGS

For external use only. Flammable. Keep away from heat or flame

Do not use

- in children less than 2 months of age
- on open skin wounds

When using this product keep out of eyes, ears, and mouth. In case of contact with eyes, rinse eyes thoroughly with water.
Stop use and ask a doctor if irritation or rash occurs. These may be signs of a serious condition.
Keep out of reach of children. If swallowed, get medical help or contact a Poison Control Center right away.

Stop use and ask a doctor if irritation or rash occurs. These may be signs of a serious condition.

Keep out of reach of children. If swallowed, get medical help or contact a Poison Control Center right away.

ACTIVE INGREDIENT

Alcohol 80% v/v. Purpose: Antiseptic

PURPOSE

Antiseptic, Hand Sanitizer

INACTIVE INGREDIENT

glycerin, purified water USP

INDICATIONS AND USAGE

Hand Sanitizer to help reduce bacteria that potentially can cause disease. For use when soap and water are not available.

Keep out of reach of children. If swallowed, get medical help or contact a Poison Control Center right away.

PACKAGE LABEL

OLIVIA CARE since 1996

All Natural HAND SANITIZER

Crafted in CA, USA for quick on-the-go clean!

vegan, cruelty-free, no sulfates or parabens.

natural ingredients

eliminates 99.9% of germs.

Purifying Lavender

4 fl oz / 118 ml